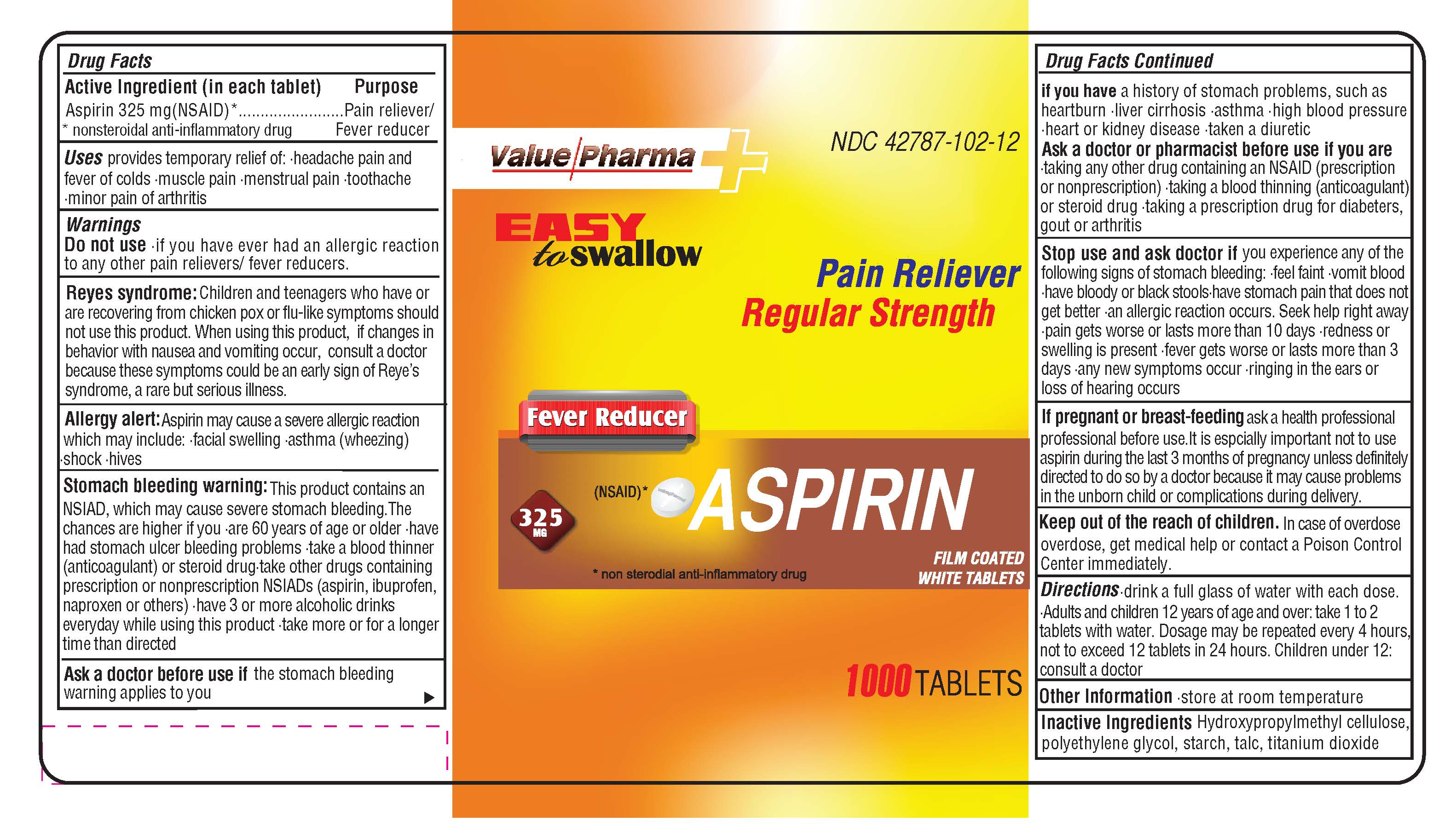 DRUG LABEL: Value PharmaPain Reliever
NDC: 42787-102 | Form: TABLET
Manufacturer: Ajes Pharmaceuticals,LLC
Category: otc | Type: HUMAN OTC DRUG LABEL
Date: 20140525

ACTIVE INGREDIENTS: Aspirin 325 mg/325 mg
INACTIVE INGREDIENTS: HYPROMELLOSES; POLYETHYLENE GLYCOLS; STARCH, CORN; talc; Titanium Dioxide

Drug Facts

Active Ingredient (in each tablet)

Aspirin 325 mg (NSAID)*

nonsteroidal antiinflammatory drug

INACTIVE INGREDIENT

Inactive Ingredients Hydroxypropylmethyl cellulose, polyethylene glycol, starch, talc, titanium dioxide

Purpose

Pain reliever / Fever reducer

KEEP OUT OF REACH OF CHILDREN

Keep out of the reach of children. In case of overdose, get medical help or contact a Poison Control Center immediately

INDICATIONS AND USAGE

Uses provides temporary relief of: headache pain and fever of colds - muscle pain - toothache - minor pain of arthritis

Warnings

Do not use - if you have ever had an allergic reaction to any other pain relievers/fever reducers.

Reyes Syndrome: Children and teenagers who have or are recovering from chicken pox or flu-like symptoms should not use this product. When using this product, if changes in behavior with nausea or vomiting occur, consult a doctor because these symptoms could be an early sign of Reye's Syndrome, a rare but serious illness.

Allergy Alert: Aspirin may cause a sever allergic reaction which may include : facial swelling - asthma (wheezing) - shock - hives

Stomach bleeding warning: This product contains an NSAID, which may cause severe stomach bleeding. The chances are higher if you are- 60 years of age or older - have had stomach ulcer bleeding problems - take a blood thinner (anticoagulant) or steroid drug - take other drugs containing prescription or non prescription NSAIDs (aspirin, ibuprofen, naproxen, others) - have 3 or more alcoholic drinks everyday while using this product - take more or for a longer time than directed

DOSAGE AND ADMINISTRATION

Directions - drink a full glass of water with each dose - Adults and children 12 years of age and over: take 1 to 2 tablets with water. Dosage may be repeated every 4 hours, not to exceed 12 tablets in 24 hours. Children under 12: consult a doctor

NURSING MOTHERS

If pregnant or breast-feeding ask a health professional before use. It is especially important not to use aspirin during the last 3 months of pregnancy unless definitely directed to do so by a doctor because it may cause problems in the unborn or complications during delivery